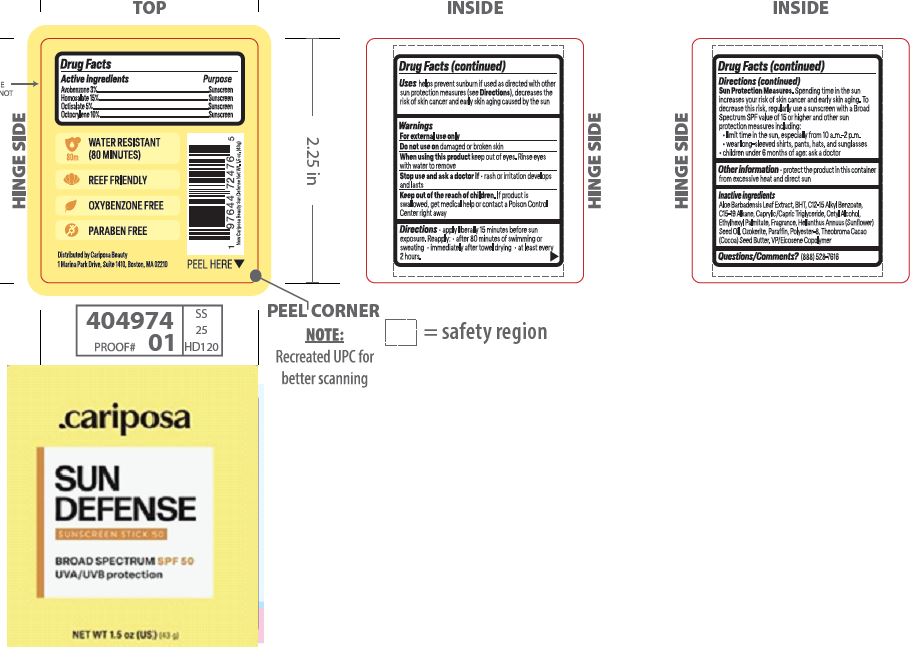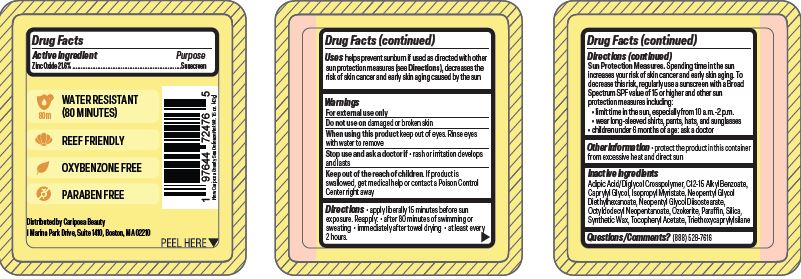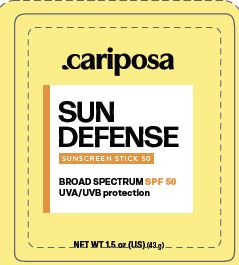 DRUG LABEL: SPF50 Sunscreen
NDC: 84267-005 | Form: STICK
Manufacturer: Talent Brands Company LLC
Category: otc | Type: HUMAN OTC DRUG LABEL
Date: 20240524

ACTIVE INGREDIENTS: OCTOCRYLENE 10 g/100 g; HOMOSALATE 15 g/100 g; OCTISALATE 5 g/100 g; AVOBENZONE 3 g/100 g
INACTIVE INGREDIENTS: C15-19 ALKANE; ETHYLHEXYL PALMITATE; CAPRYLIC/CAPRIC/LAURIC TRIGLYCERIDE; SUNFLOWER OIL; COCOA BUTTER; BUTYLATED HYDROXYTOLUENE; CETYL ALCOHOL; ALOE; PARAFFIN; ALKYL (C12-15) BENZOATE; VINYLPYRROLIDONE/EICOSENE COPOLYMER; POLYESTER-8 (1400 MW, CYANODIPHENYLPROPENOYL CAPPED)

SPF50 Sunscreen Stick

Active ingredient

Zinc Oxide 21.6% ................Sunscreen

Purpose

Sunscreen

Uses

helps prevent sunburn if used as directed with other
sun protection measures (see Directions), decreases the
risk of skin cancer and early skin aging caused by the sun

Do not use on

damaged or broken skin

When using this product

keep out of eyes. Rinse eyes with water to remove

Stop use and ask a doctor if

• rash or irritation develops and lasts

Keep out of the reach of children

If product is swallowed, get medical help or contact a Poison Control Center right away

Directions

apply liberally 15 minutes before sun exposure. Reapply: • after 80 minutes of swimming or sweating • immediately after towel drying • at least every 2 hours. Sun Protection Measures.Spending time in the sun increases your risk of skin cancer and early skin aging. To decrease this risk, regularly use a sunscreen with a Broad Spectrum SPF value of 15 or higher and other sun protection measures including: • limit time in the sun, especially from 10 a.m.-2 p.m. • wear long-sleeved shirts, pants, hats, and sunglasses • children under 6 months of age: ask a doctor

Other information

protect the product in this container from excessive heat and direct sun

Inactive ingredients

Adipic Acid/Diglycol Crosspolymer, C12-15 Alkyl Benzoate,
Caprylyl Glycol, Isopropyl Myristate, Neopentyl Glycol
Diethylhexanoate, Neopentyl Glycol Diisostearate,
Octyldodecyl Neopentanoate, Ozokerite, Paraffin, Silica,
Synthetic Wax, Tocopheryl Acetate, Triethoxycaprylylsilane